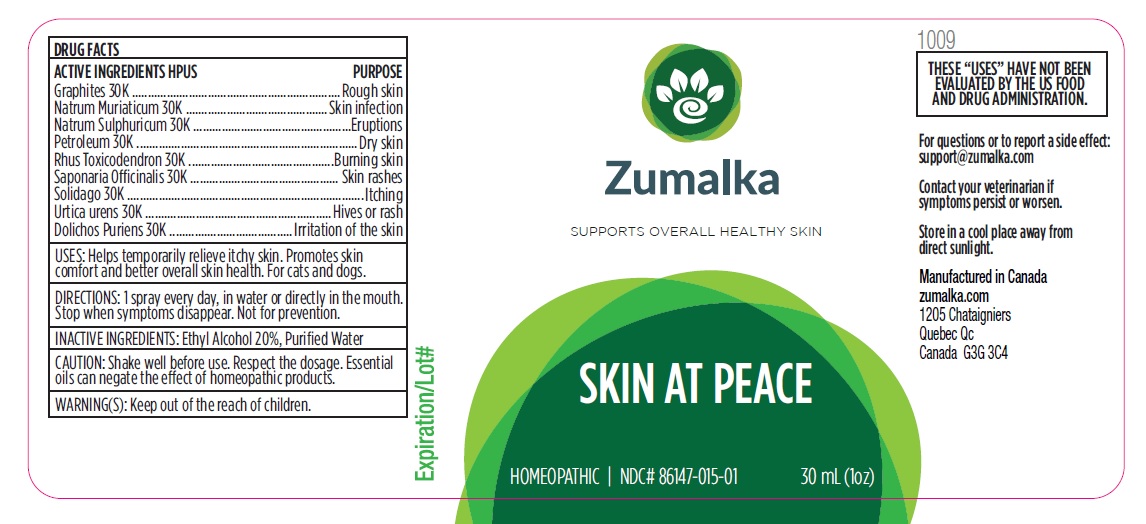 DRUG LABEL: SKIN AT PEACE
NDC: 86147-015 | Form: LIQUID
Manufacturer: Groupe Cyrenne Inc.
Category: homeopathic | Type: OTC ANIMAL DRUG LABEL
Date: 20251120

ACTIVE INGREDIENTS: GRAPHITE 30 [kp_C]/30 mL; SODIUM SULFATE 30 [kp_C]/30 mL; SODIUM CHLORIDE 30 [kp_C]/30 mL; LIQUID PETROLEUM 30 [kp_C]/30 mL; SOLIDAGO VIRGAUREA FLOWERING TOP 30 [kp_C]/30 mL; MUCUNA PRURIENS FRUIT TRICHOME 30 [kp_C]/30 mL; TOXICODENDRON PUBESCENS LEAF 30 [kp_C]/30 mL; SAPONARIA OFFICINALIS ROOT 30 [kp_C]/30 mL; URTICA URENS WHOLE 30 [kp_C]/30 mL
INACTIVE INGREDIENTS: WATER; ALCOHOL

Active ingredient Purpose

Graphites 30k Rough skin

Natrum Sulphuricum 30k Eruptions

Natrum Muriaticum 30k Skin infection

Petroleum 30k Dry skin

Rhus Toxicodendron 30k Burning skin

Saponaria Officinalis 30k Skin rashes

Solidago 30k Itching

Urtica Urens 30k Hives or rash

Dolichos Puriens 30k Irritation of the skin

Uses

Heps temporarily relieve itchy skin. Promotes skin comfort and better overall skin health. For cats and dogs.

Warnings

Shake well before use. Respect the dosage. Keep out of reach of children.

Direction

1 spray every day, in water or directly in the mouth. Stop when symptoms disappear. Not for prevention.

Inactive ingredient

Ethyl alcohol 20%, purified water

Cautions

Shake well before use. Respect the dosage. Essential oils can negate the effects of homeopathic products. Store in a cool place away from direct sunlight.

For questions or to report a side effect

support@zumalka.com Contact your veterinarian if symptoms persist or worsen.